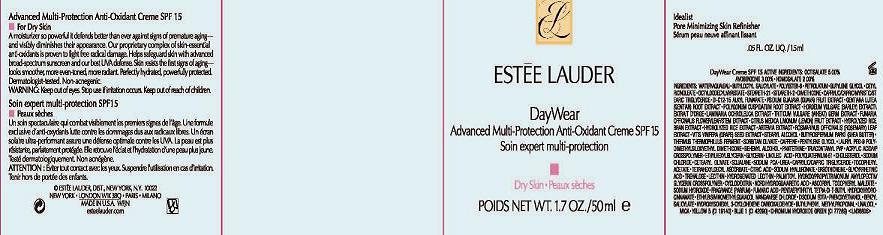 DRUG LABEL: DAYWEAR
NDC: 11559-007 | Form: CREAM
Manufacturer: ESTEE LAUDER INC
Category: otc | Type: HUMAN OTC DRUG LABEL
Date: 20101218

ACTIVE INGREDIENTS: OCTISALATE 5.0 mL/100 mL; AVOBENZONE 3.0 mL/100 mL; HOMOSALATE 2.0 mL/100 mL
INACTIVE INGREDIENTS: WATER; PETROLATUM; BUTYLENE GLYCOL; DIMETHICONE; SHEA BUTTER; GLYCERIN; CHOLESTEROL; SQUALANE; CITRIC ACID MONOHYDRATE; LECITHIN, SOYBEAN; BUTYLATED HYDROXYTOLUENE; PHENOXYETHANOL

ACTIVE INGREDIENT

ACTIVE INGREDIENTS: OCTISALATE 5.00% [] AVOBENZONE 3.00% [] HOMOSALATE 2.00%

INACTIVE INGREDIENT

INACTIVE INGREDIENTS: WATER\AQUA\EAU [] BUTYLOCTYL SALICYLATE [] POLYESTER-8 [] PETROLATUM [] BUTYLENE GLYCOL [] CETYL RICINOLEATE [] OCTYLDODECYL MYRISTATE [] STEARETH-21 [] STEARETH-2 [] CAPRYLIC/CAPRIC/MYRISTIC/STEARIC TRIGLYCERIDE [] DI-C12-15 ALKYL FUMARATE [] DIMETHICONE [] PSIDIUM GUAJAVA (GUAVA) FRUIT EXTRACT [] GENTIANA LUTEA (GENTIAN) ROOT EXTRACT [] POLYGONUM CUSPIDATUM ROOT EXTRACT [] HORDEUM VULGARE (BARLEY) EXTRACT\EXTRAIT D'ORGE [] LAMINARIA OCHROLEUCA EXTRACT [] TRITICUM VULGARE (WHEAT) GERM EXTRACT [] FUMARIA OFFICINALIS FLOWER/LEAF/STEM EXTRACT [] CITRUS MEDICA LIMONUM (LEMON) FRUIT EXTRACT [] HYDROLYZED RICE BRAN EXTRACT [] HYDROLYZED RICE EXTRACT [] ARTEMIA EXTRACT [] ROSMARINUS OFFICINALIS (ROSEMARY) LEAF EXTRACT [] VITIS VINIFERA (GRAPE) SEED EXTRACT [] STEARYL ALCOHOL [] BUTYROSPERMUM PARKII (SHEA BUTTER) [] THERMUS THERMOPHILLUS FERMENT [] SORBITAN OLIVATE [] CAFFEINE [] PENTYLENE GLYCOL [] LAURYL PEG-9 POLYDIMETHYLSILOXYETHYL DIMETHICONE [] BEHENYL ALCOHOL [] PANTETHINE [] TRIACONTANYL PVP [] ACRYLIC ACID/VP CROSSPOLYMER [] ETHYLHEXYLGLYCERIN [] GLYCERIN [] LINOLEIC ACID [] POLYQUATERNIUM-51 [] CHOLESTEROL [] CETEARYL OLIVATE [] SQUALANE [] SODIUM PCA [] UREA [] CAPRYLIC/CAPRIC TRIGLYCERIDE [] TOCOPHERYL ACETATE [] TETRAHEXYLDECYL ASCORBATE [] CITRIC ACID [] SODIUM HYALURONATE [] ERGOTHIONEINE [] GLYCYRRHETINIC ACID [] TREHALOSE [] LECITHIN [] HYDROGENATED LECITHIN [] PALMITOYL HYDROXYPROPYLTRIMONIUM AMYLOPECTIN/GLYCERIN CROSSPOLYMER [] CYCLODEXTRIN [] NORDIHYDROGUAIARETIC ACID [] ASCORBYL TOCOPHERYL MALEATE [] SODIUM HYDROXIDE [] FRAGRANCE (PARFUM) [] FUMARIC ACID [] PENTAERYTHRITYL TETRA-DI-T-BUTYL HYDROXYHYDROCINNAMATE [] ETHYLBISIMINOMETHYLGUAIACOL MANGANESE CHLORIDE [] DISODIUM EDTA [] BHT [] PHENOXYETHANOL [] BENZYL SALICYLATE [] HYDROXYISOHEXYL 3-CYCLOHEXENE CARBOXALDEHYDE [] BUTYLPHENYL METHYLPROPIONAL [] LINALOOL [] MICA [] YELLOW 5 (CI 19140) [] BLUE 1 (CI 42090) [] CHROMIUM HYDROXIDE GREEN (CI 77289)

WARNINGS

WARNING: KEEP OUT OF EYES. DISCONTINUE USE IF IRRITATION OCCURS.

KEEP OUT OF REACH OF CHILDREN.

PACKAGE LABEL

PRINCIPAL DISPLAY PANEL

ESTEE LAUDER

DAYWEAR

ADVANCED MULTI-PROTECTION ANTI-OXIDANT CREME

SPF 15

FOR DRY SKIN

1.7 FL OZ/50 ML

ESTEE LAUDER DISTR

NY NY 10022